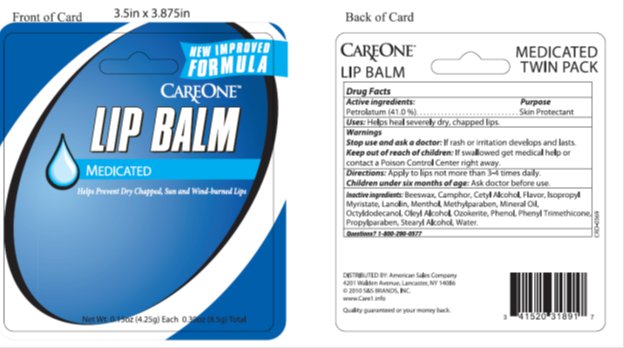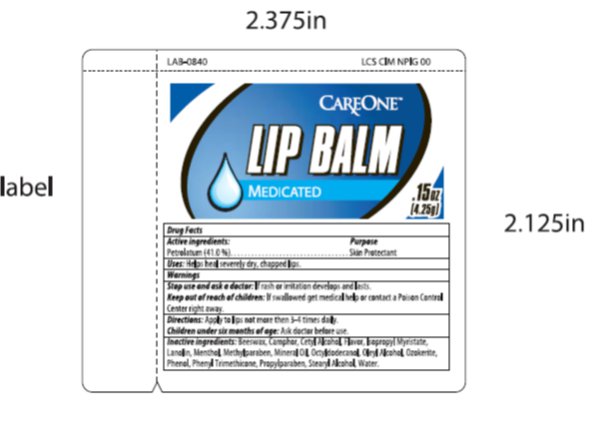 DRUG LABEL: Care One Medicated Lip Balm
NDC: 41520-975 | Form: STICK
Manufacturer: American Sales Company
Category: otc | Type: HUMAN OTC DRUG LABEL
Date: 20130311

ACTIVE INGREDIENTS: PETROLATUM 41 mg/1 g
INACTIVE INGREDIENTS: CERESIN 16 mg/1 g; APIS CERANA WORKER SECRETION 6 mg/1 g; OLEYL ALCOHOL 6 mg/1 g; ISOPROPYL MYRISTATE 5 mg/1 g; OCTYLDODECANOL 9 mg/1 g; LANOLIN 4 mg/1 g; STEARYL ALCOHOL 3 mg/1 g; CETYL ALCOHOL 3 mg/1 g; LIGHT MINERAL OIL 3 mg/1 g; MENTHOL .60 mg/1 g

Drug Facts

Active ingredient

Petrolatum

Purpose

Skin Protectant

Keep Out of Reach of Children

If swallowed get medical help or contact a Poison Control Center right away.

Uses

Helps heal severely dry, chapped lips.

Warnings

Stop use and ask a doctor: if rash or irritation develops and lasts.

Directions

Apply to lips not more than 3 – 4 times daily. Children under six months of age: Ask doctor before use.

Inactive Ingredients

Beeswax, Camphor, Cetyl Alcohol, Flavor, Ispropyl Myristate, Lanolin, Menthol, Methylparaben, Mineral Oil, Octyldodecanol, Oleyl Alcohol, Ozokerite, Phenol, Phenyl Trimethicone, Propylparaben, Stearyl Alcohol, Water